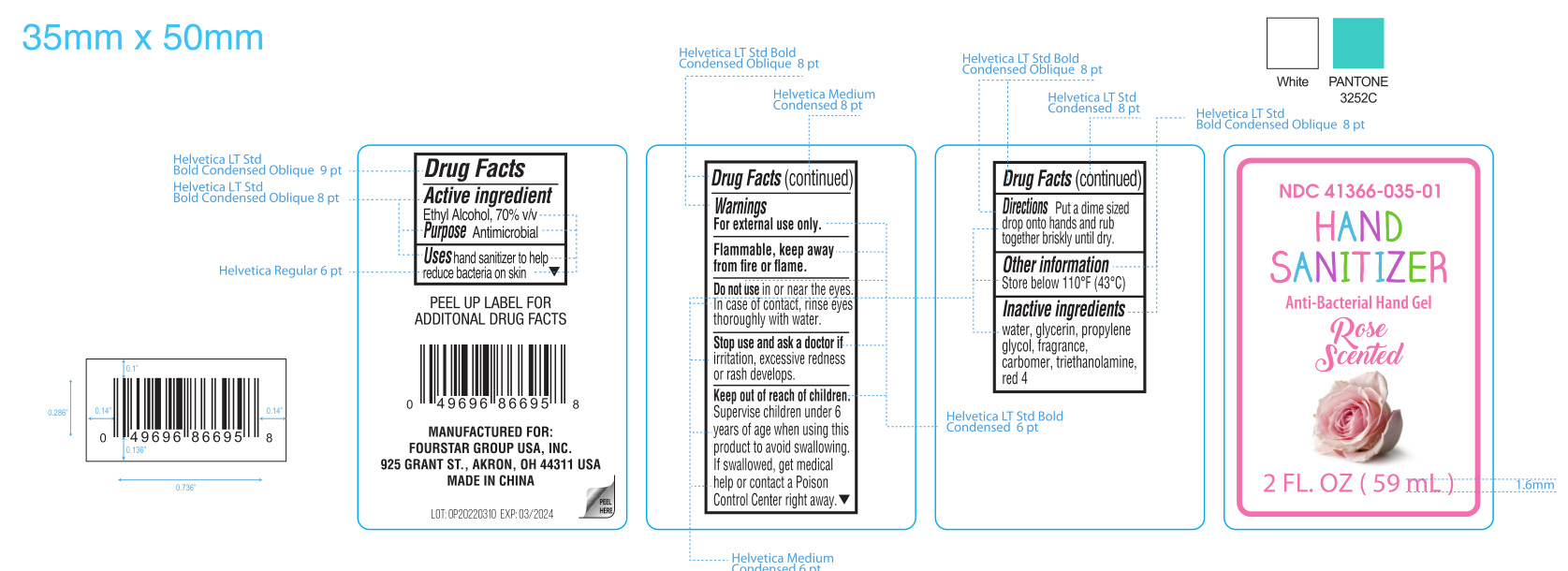 DRUG LABEL: Hand Sanitizer
NDC: 41366-055 | Form: GEL
Manufacturer: Zhejiang Meimi Technology Co., Ltd.
Category: otc | Type: HUMAN OTC DRUG LABEL
Date: 20251206

ACTIVE INGREDIENTS: ALCOHOL 70 mL/100 mL
INACTIVE INGREDIENTS: FD&C RED NO. 4; TROLAMINE; WATER; PROPYLENE GLYCOL; GLYCERIN; CARBOMER 940; ROSA RUGOSA FLOWER BUD

Zhejiang Meimi Technology Co., Ltd.
Hand Sanitizer
41366-055-01

Active Ingredient(s)

Ethyl Alcohol 70% v/v

Purpose

Antimicrobial

Use

Uses hand sanitizer to help reduce bacteria on skin.

Warnings

- For external use only.
- Flammable. Keep away from heat or flame.

Do not use in or near the eyes. In case of contact, rinse eyes thoroughly with water.

Stop use and ask a doctor if irritation, excessive redness or rash develops.

Keep out of reach of children. Supervise children under 6 years of age when using this product to avoid swallowing. If swallowed, get medical help or contact a Poison Control Center right away.

Directions

Put a dime sized drop onto hands and rub together briskly until dry.

Other information

Store below 110℉(43℃).

Inactive ingredients

Water, glycerin, propylene glycol, fragrance, carbomer, triethanolamine, red 4.

Package Label - Principal Display Panel

59 mL in 1 BOTTLE

NDC: 41366-055-01